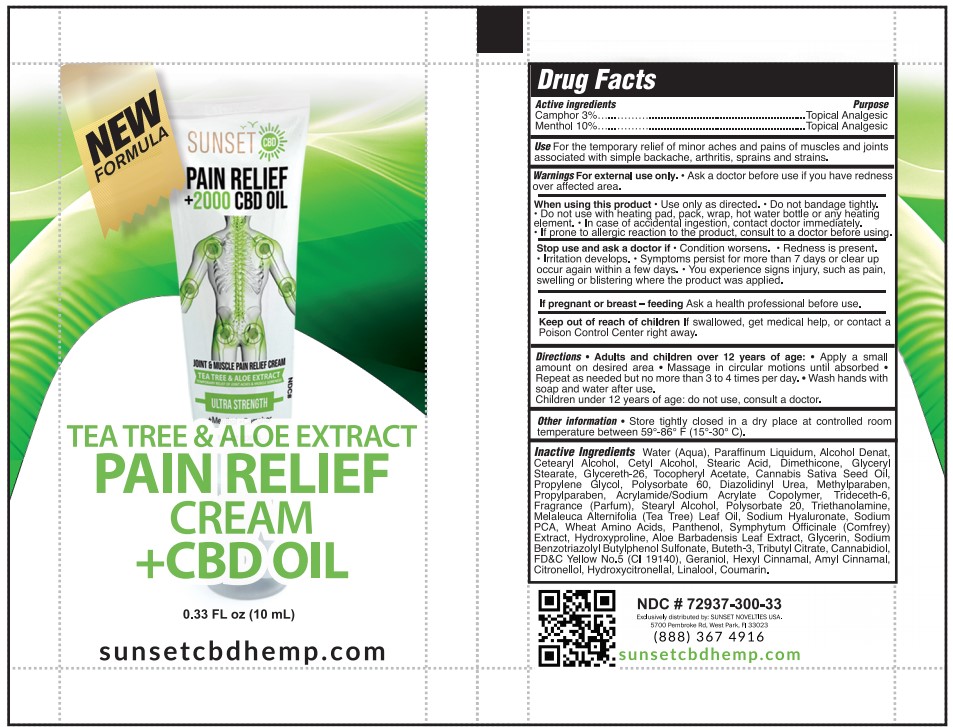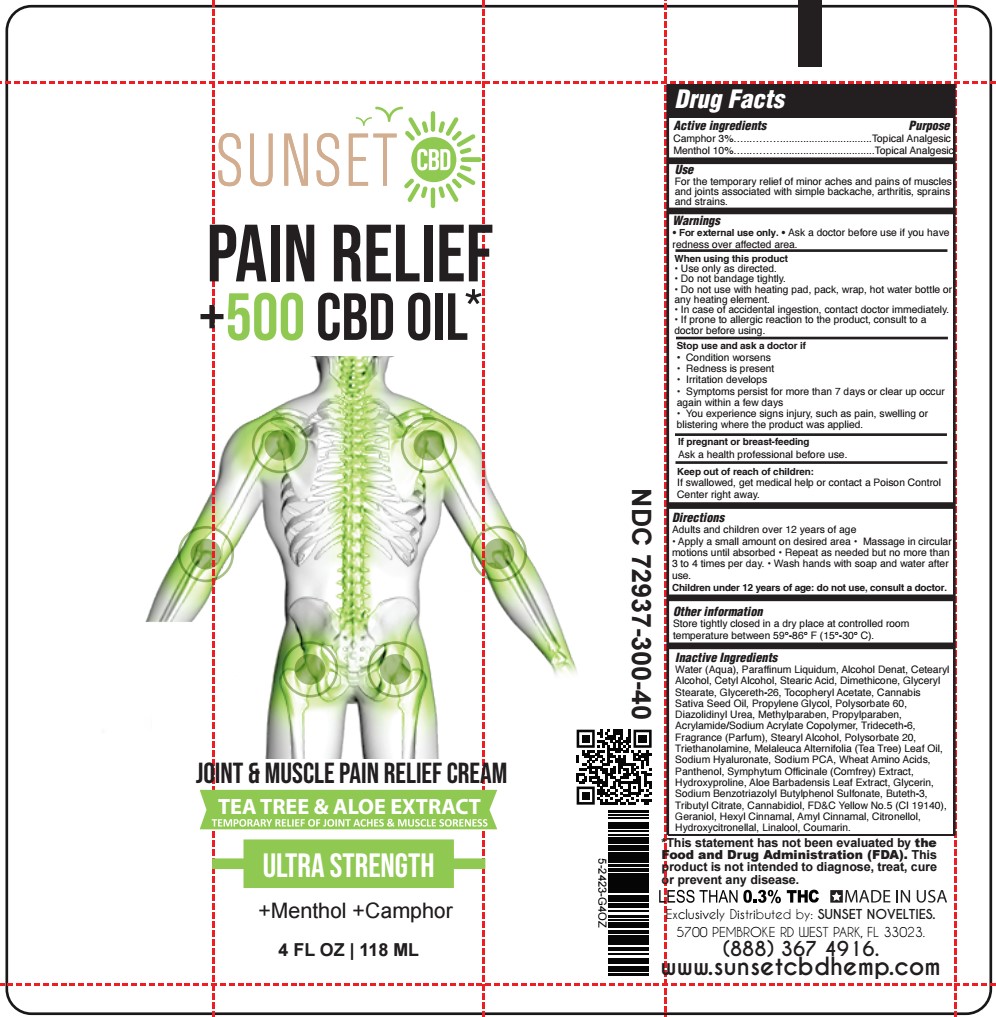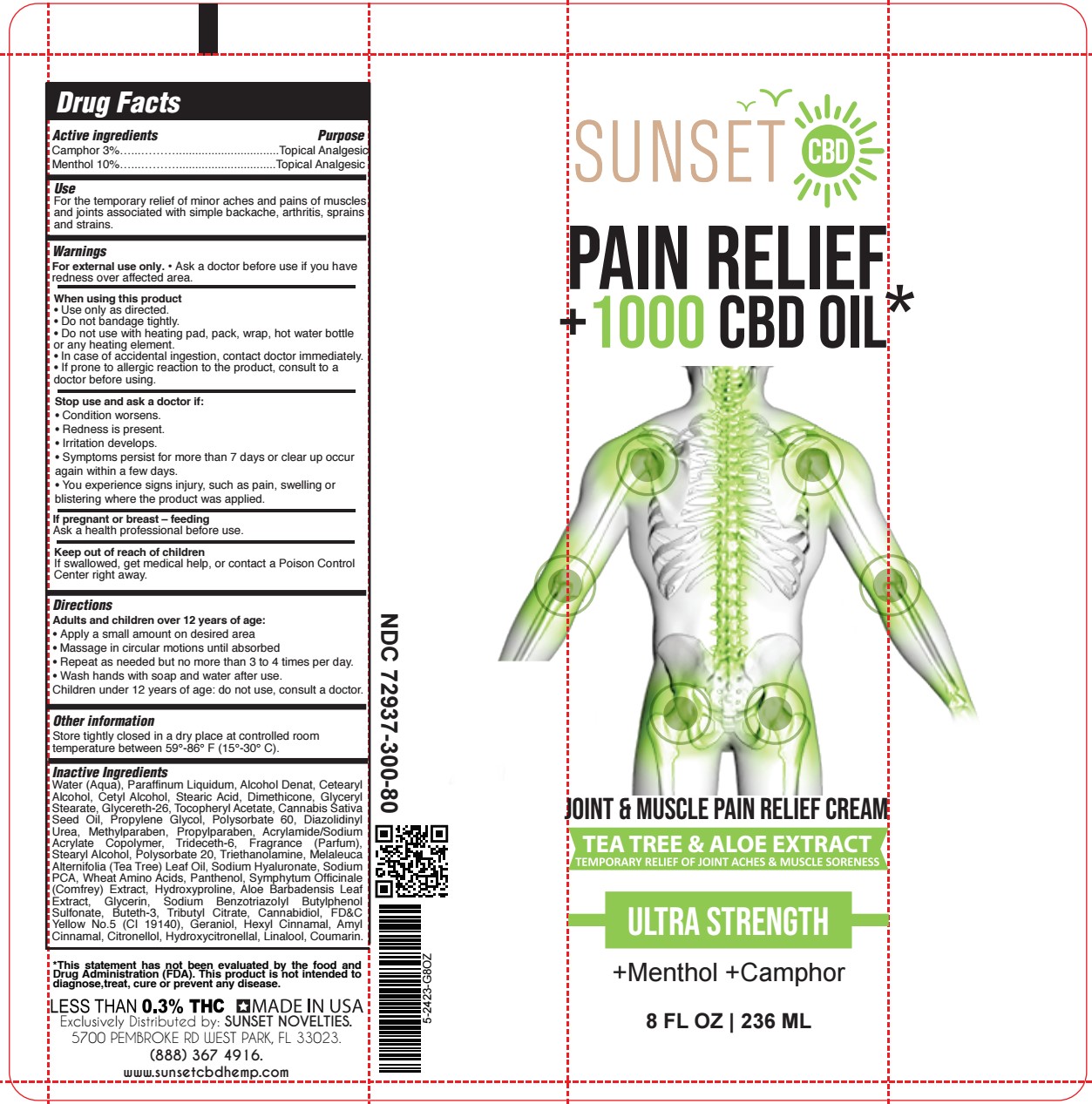 DRUG LABEL: MENTHOL, CAMPHOR
NDC: 72937-300 | Form: CREAM
Manufacturer: SUNSET NOVELTIES, INC
Category: otc | Type: HUMAN OTC DRUG LABEL
Date: 20251120

ACTIVE INGREDIENTS: MENTHOL, UNSPECIFIED FORM 10 g/100 g; CAMPHOR (NATURAL) 3 g/100 g
INACTIVE INGREDIENTS: CANNABIDIOL; PROPYLENE GLYCOL; .ALPHA.-AMYLCINNAMALDEHYDE; .ALPHA.-HEXYLCINNAMALDEHYDE; WATER; MINERAL OIL; CETOSTEARYL ALCOHOL; PROPYLPARABEN; TROLAMINE; LINALOOL, (+/-)-; STEARIC ACID; GLYCERYL STEARATE SE; GLYCERETH-26; DIAZOLIDINYL UREA; METHYLPARABEN; CANNABIS SATIVA SEED OIL; TRIDECETH-6; TEA TREE OIL; GERANIOL; HYDROXYCITRONELLAL; COUMARIN; COMFREY LEAF; BUTETH-3; AMINO ACIDS, WHEAT; CETYL ALCOHOL; .ALPHA.-TOCOPHEROL ACETATE; SODIUM PYRROLIDONE CARBOXYLATE; HYDROXYPROLINE; GLYCERIN; TRIBUTYL CITRATE; ALOE VERA LEAF; DIMETHICONE 1000; POLYSORBATE 60; STEARYL ALCOHOL; POLYSORBATE 20; HYALURONATE SODIUM; ALCOHOL; FD&C YELLOW NO. 5; SODIUM BENZOTRIAZOLYL BUTYLPHENOL SULFONATE; PANTHENOL

72937-300-40
72937-300-80
72937-300-33

ACTIVE INGREDIENT

Menthol 10%

Camphor 3%

PURPOSE

Topical Analgesic

USES:

For the temporary relief of minor aches and pains of muscles and joints associated with simple backache, arthritis, sprains and strains.

WARNINGS

For external use only. · Ask a doctor before use if you have redness over affected area

WHEN USING

Use only as directed.
Do not bandage tightly.
Do not use with heating pad, pack, wrap, hot water bottle or any heating element.
In case of accidental ingestion, contact doctor immediately.

If prone to allergic reaction to the product, consult to a doctor before using.

STOP USE

Condition worsens.
Redness is present.
Irritation develops.
Symptoms persist for more than 7 days or clear up occur again within a few days.

You experience signs injury, such as pain, swelling or blistering where the product was applied.

KEEP OUT OF REACH OF CHILDREN

If swallowed, get medical help or contact a Poison Control Center right away.

If pregnant or breast – feeding

Ask a health professional before use.

DIRECTIONS:

Adults and Children over 12 years

Apply a small amount on desired area.
Massage in circular motions until absorbed.
Repeat as needed, but no more than 3 to 4 times per day.
Wash hands with soap and water after use.

Children under 12 years of age: do not use, consult a doctor.

OTHER SAFETY INFORMATION

Store tightly closed in a dry place at controlled room temperature between 59°-86° F (15°-30° C).

INACTIVE INGREDIENT

Water (Aqua), Paraffinum Liquidum, Alcohol Denat, Cetearyl Alcohol, Cetyl Alcohol, Stearic Acid, Dimethicone, Glyceryl Stearate, Glycereth-26, Tocopheryl Acetate, Cannabis Sativa Seed Oil, Propylene Glycol, Polysorbate 60, Diazolidinyl Urea, Methylparaben, Propylparaben, Acrylamide/Sodium Acrylate Copolymer, Trideceth-6, Fragrance (Parfum), Stearyl Alcohol, Polysorbate 20, Triethanolamine, Melaleuca Alternifolia (Tea Tree) Leaf Oil, Sodium Hyaluronate, Sodium PCA, Wheat Amino Acids, Panthenol, Symphytum Officinale (Comfrey) Extract, Hydroxyproline, Aloe Barbadensis Leaf Extract, Glycerin, Sodium Benzotriazolyl Butylphenol Sulfonate, Buteth-3, Tributyl Citrate, Cannabidiol, FD&C Yellow No.5 (CI 19140), Geraniol, Hexyl Cinnamal, Amyl Cinnamal, Citronellol, Hydroxycitronellal, Linalool, Coumarin.